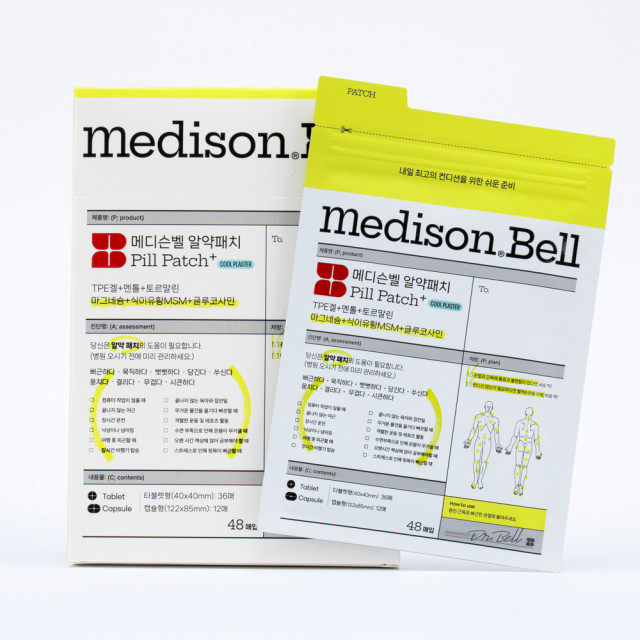 DRUG LABEL: Medison Bell Pill Patch
NDC: 71829-0010 | Form: KIT | Route: TOPICAL
Manufacturer: SENNY STUDIO Co., Ltd
Category: otc | Type: HUMAN OTC DRUG LABEL
Date: 20241225

ACTIVE INGREDIENTS: GLUCOSAMINE 0.0045 g/1 1; DIMETHYL SULFONE 0.0045 g/1 1; MAGNESIUM SULFATE 0.0135 g/1 1; GLUCOSAMINE 0.0155 g/1 1; DIMETHYL SULFONE 0.0155 g/1 1; MAGNESIUM SULFATE 0.045 g/1 1
INACTIVE INGREDIENTS: MINERAL OIL; MENTHOL; MINERAL OIL; MENTHOL

Drug Facts

ACTIVE INGREDIENT

Tourmaline, Magnesium sulfate, Dimethyl Sulfone, Glucosamine

PURPOSE

Effective for relieving muscle stiffness and joint pain.

INDICATIONS AND USAGE

For external use only

WARNINGS

1. Do not use if you have skin conditions, eczema, or allergies.
2. If you experience swelling, pain, or red spots on the skin during use, stop using immediately and consult a physician.
3. Recommended use is up to 8 hours per day.
4. Store any unused patches in the resealable pouch to maintain effectiveness.
5. Keep out of reach of infants and children.
6. Do not use for purposes other than intended, and keep away from fire.
7. Avoid storing in temperatures above 30°C or in direct sunlight.

Keep out of reach of children.

DOSAGE AND ADMINISTRATION

1. Please clean the application area to remove any moisture or debris before use.
2. Peel the patch from the transparent film and place it on the desired area, pressing down firmly around the edges.

INACTIVE INGREDIENT

Mineral Oil, Hydrogenated polycyclopentadiene, Hydrogenated Styrene/Butadiene Copolymer, Menthol,